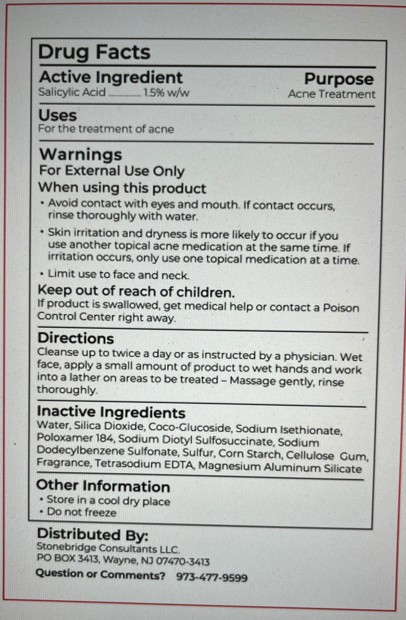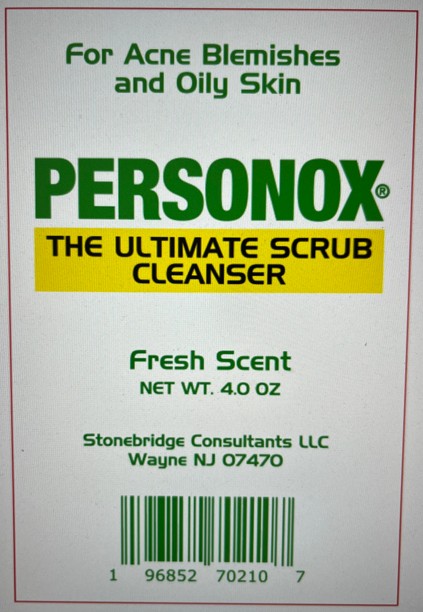 DRUG LABEL: Personox Ultimate Scrub Cleanser
NDC: 83044-101 | Form: CREAM
Manufacturer: Stonebridge Consultants LLC
Category: otc | Type: HUMAN OTC DRUG LABEL
Date: 20251112

ACTIVE INGREDIENTS: SALICYLIC ACID 1.5 g/100 g
INACTIVE INGREDIENTS: SILICON DIOXIDE; COCO-GLUCOSIDE; SULFUR; EDETATE SODIUM; MAGNESIUM ALUMINUM SILICATE; DOCUSATE SODIUM; STARCH, CORN; SODIUM DODECYLBENZENESULFONATE; WATER; SODIUM ISETHIONATE; POLOXAMER 184; CARBOXYMETHYLCELLULOSE SODIUM, UNSPECIFIED

Personox (as PLD) - Ultimate Scrub Cleanser (83044-101)

ACTIVE INGREDIENT

SALICYLIC ACID.......... 1.5% W/W

PURPOSE

ACNE TREATMENT

USES

FOR THE TREATMENT OF ACNE

WARNINGS

FOR EXTERNAL USE ONLY

WHEN USING THIS PRODUCT

- AVOID CONTACT WITH EYES AND MOUTH. IF CONTACT OCCURS, RINSE THOROUGHLY WITH WATER.
- SKIN IRRITATION AND DRYNESS IS MORE LIKELY TO OCCUR IF YOU USE ANOTHER TOPICAL ACNE MEDICATION AT THE SAME TIME. IF IRRITATION OCCURS, ONLY USE ONE TOPICAL MEDICATION AT A TIME.
- LIMIT USE TO FACE AND NECK.

KEEP OUT OF REACH OF CHILDREN.

IF PRODUCT IS SWALLOWED, GET MEDICAL HELP OR CONTACT A POISON CONTROL CENTER RIGHT AWAY.

DIRECTIONS

CLEANSE UP TO TWICE A DAY OR AS INSTRUCTED BY A PHYSICIAN. WET FACE, APPLY A SMALL AMOUNT OF PRODUCT TO WET HANDS AND WORK INTO A LATHER ON AREAS TO BE TREATED - MASSAGE GENTLY, RINSE THOROUGHLY.

INACTIVE INGREDIENTS

WATER, SILICA DIOXIDE, COCO-GLUCOSIDE, SODIUM ISETHIONATE, POLOXAMER 184, SODIUM DIOCTYL SULFOSUCCINATE, SODIUM DODECYLBENZENESULFONATE, SULFUR, CORN STARCH, CELLULOSE GUM, FRAGRANCE, TETRASODIUM EDTA, MAGNESIUM ALUMINUM SILICATE

OTHER INFORMATION

- STORE IN A COOL DRY PLACE
- DO NOT FREEZE